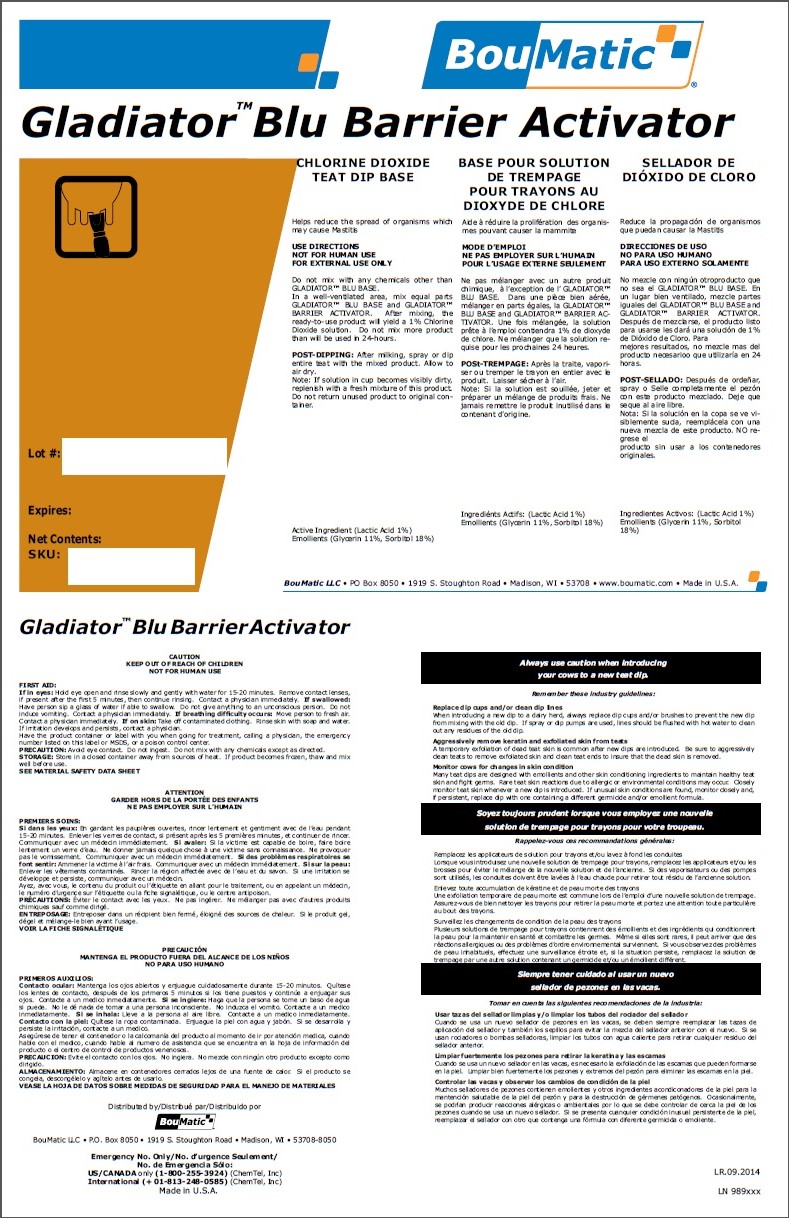 DRUG LABEL: Gladiator BLU Barrier Activator
NDC: 48106-1312 | Form: LIQUID
Manufacturer: BouMatic, LLC
Category: animal | Type: OTC ANIMAL DRUG LABEL
Date: 20141001

ACTIVE INGREDIENTS: LACTIC ACID 8.8 g/1 L
INACTIVE INGREDIENTS: UREA 10 g/1 L; GLYCERIN 110 g/1 L

Gladiator BLU Barrier Activator

INDICATIONS AND USAGE

CHLORINE DIOXIDE TEAT DIP BASE

Helps reduce the spread of organisms which may cause Mastitis

USE DIRECTIONS
NOT FOR HUMAN USE
FOR EXTERNAL USE ONLY

Do not mix with any chemicals other than GLADIATOR™ BLU BASE.
In a well-ventilated area, mix equal parts GLADIATOR™ BLU BASE and GLADIATOR™
BARRIER ACTIVATOR. After mixing, the ready-to-use product will yield a 1% Chlorine
Dioxide solution. Do not mix more product than will be used in 24-hours.

POST-DIPPING: After milking, spray or dip entire teat with the mixed product. Allow to
air dry.

Note: If solution in cup becomes visibly dirty,replenish with a fresh mixture of this product.

Do not return unused product to original container.

SAFE HANDLING WARNING

CAUTION

KEEP OUT OF REACH OF CHILDREN

NOT FOR HUMAN USE

FIRST AID:
If in eyes: Hold eye open and rinse slowly and gently with water for 15-20 minutes. Remove contact lenses,
if present after the first 5 minutes, then continue rinsing. Contact a physician immediately.

If swallowed: Have person sip a glass of water if able to swallow. Do not give anything to an unconscious person. Do not
induce vomiting. Contact a physician immediately.

If breathing difficulty occurs: Move person to fresh air. Contact a physician immediately.

If on skin: Take off contaminated clothing. Rinse skin with soap and water. If irritation develops and persists, contact a physician.

Have the product container or label with you when going for treatment, calling a physician, the emergency
number listed on this label or MSDS, or a poison control center.

PRECAUTION: Avoid eye contact. Do not ingest. Do not mix with any chemicals except as directed.

STORAGE: Store in a closed container away from sources of heat. If product becomes frozen, thaw and mix
well before use.

SEE MATERIAL SAFETY DATA SHEET